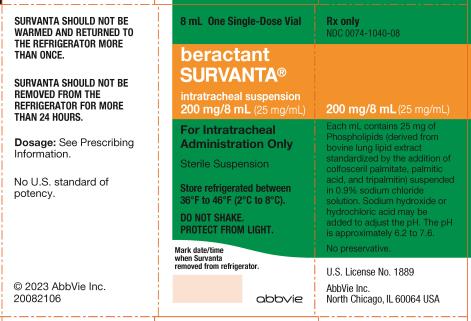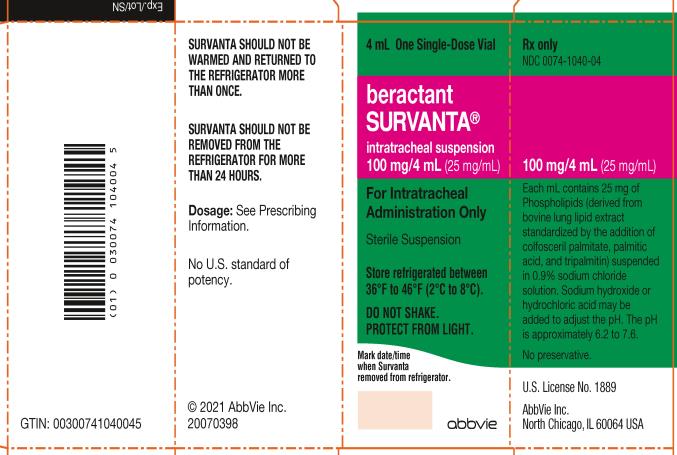 DRUG LABEL: Survanta
NDC: 0074-1040 | Form: SUSPENSION
Manufacturer: AbbVie Inc.
Category: prescription | Type: HUMAN PRESCRIPTION DRUG LABEL
Date: 20201015

ACTIVE INGREDIENTS: BERACTANT 25 mg/1 mL
INACTIVE INGREDIENTS: COLFOSCERIL PALMITATE; TRIPALMITIN; PALMITIC ACID; SODIUM CHLORIDE; WATER; SODIUM HYDROXIDE; HYDROCHLORIC ACID

SURVANTA
(beractant)
intratracheal suspension
Sterile Suspension
For Intratracheal Administration Only

DESCRIPTION

SURVANTA® contains beractant, a pulmonary surfactant, which is a natural bovine lung extract containing phospholipids, neutral lipids, fatty acids, and surfactant-associated proteins (SP) to which colfosceril palmitate (dipalmitoylphosphatidylcholine), palmitic acid, and tripalmitin are added to standardize the composition and to mimic surface-tension lowering properties of natural lung surfactant. The resulting composition provides 25 mg/mL of phospholipids (including 11.0-15.5 mg/mL of disaturated phosphatidylcholine), 0.5-1.75 mg/mL of triglycerides, 1.4-3.5 mg/mL of free fatty acids, and less than 1 mg/mL of SP (including SP-B, a 79-amino acid protein, and SP-C, a 35-amino acid peptide).

SURVANTA (beractant) intratracheal suspension is a sterile, preservative-free, non-pyrogenic off-white to light brown liquid supplied in single-dose glass vials for intratracheal use only. Each vial contains 4 mL (100 mg phospholipids) or 8 mL (200 mg phospholipids). Each mL of SURVANTA contains 25 mg of phospholipids. It is suspended in 0.9% sodium chloride solution and heat-sterilized. SURVANTA contains no preservatives. Sodium hydroxide or hydrochloric acid may be added to adjust the pH. The pH is approximately 6.2 to 7.6.

CLINICAL PHARMACOLOGY

Endogenous pulmonary surfactant lowers surface tension on alveolar surfaces during respiration and stabilizes the alveoli against collapse at resting transpulmonary pressures. Deficiency of pulmonary surfactant causes Respiratory Distress Syndrome (RDS) in premature infants. SURVANTA replenishes surfactant and restores surface activity to the lungs of these infants.

Activity

In vitro, SURVANTA reproducibly lowers minimum surface tension to less than 8 dynes/cm as measured by the pulsating bubble surfactometer and Wilhelmy Surface Balance. In situ, SURVANTA restores pulmonary compliance to excised rat lungs artificially made surfactant-deficient. In vivo, single SURVANTA doses improve lung pressure-volume measurements, lung compliance, and oxygenation in premature rabbits and sheep.

Animal Metabolism

SURVANTA is administered directly to the target organ, the lungs, where biophysical effects occur at the alveolar surface. In surfactant-deficient premature rabbits and lambs, alveolar clearance of radio-labelled lipid components of SURVANTA is rapid. Most of the dose becomes lung-associated within hours of administration, and the lipids enter endogenous surfactant pathways of reutilization and recycling. In surfactant-sufficient adult animals, SURVANTA clearance is more rapid than in premature and young animals. There is less reutilization and recycling of surfactant in adult animals.

Limited animal experiments have not found effects of SURVANTA on endogenous surfactant metabolism. Precursor incorporation and subsequent secretion of saturated phosphatidylcholine in premature sheep are not changed by SURVANTA treatments.

No information is available about the metabolic fate of the surfactant-associated proteins in SURVANTA. The metabolic disposition in humans has not been studied.

CLINICAL STUDIES

Clinical effects of SURVANTA were demonstrated in six single-dose and four multiple-dose randomized, multi-center, controlled clinical trials involving approximately 1700 infants. Three open trials, including a Treatment IND, involved more than 8500 infants. Each dose of SURVANTA in all studies was 100 mg phospholipids/kg birth weight and was based on published experience with Surfactant TA, a lyophilized powder dosage form of SURVANTA having the same composition. SURVANTA significantly reduces the incidence of RDS, mortality due to RDS and air leak complications.

Prevention Studies

Infants of 600-1250 g birth weight and 23 to 29 weeks estimated gestational age were enrolled in two multiple-dose studies. A dose of SURVANTA was given within 15 minutes of birth to prevent the development of RDS. Up to three additional doses in the first 48 hours, as often as every 6 hours, were given if RDS subsequently developed and infants required mechanical ventilation with an FiO2 ≥ 0.30. Results of the studies at 28 days of age are shown in Table 1.

Table 1.
Study 1
 | SURVANTA | Control | P-Value
Number infants studied | 119 | 124
Incidence of RDS (%) | 27.6 | 63.5 | < 0.001
Death due to RDS (%) | 2.5 | 19.5 | < 0.001
Death or BPD due to RDS (%) | 48.7 | 52.8 | 0.536
Death due to any cause (%) | 7.6 | 22.8 | 0.001
Air Leaksa (%) | 5.9 | 21.7 | 0.001
Pulmonary interstitial emphysema (%) | 20.8 | 40.0 | 0.001

Study 2 b
 | SURVANTA | Control | P-Value
Number infants studied | 91 | 96
Incidence of RDS (%) | 28.6 | 48.3 | 0.007
Death due to RDS (%) | 1.1 | 10.5 | 0.006
Death or BPD due to RDS (%) | 27.5 | 44.2 | 0.018
Death due to any cause C(%) | 16.5 | 13.7 | 0.633
Air Leaks a(%) | 14.5 | 19.6 | 0.374
Pulmonary interstitial emphysema (%) | 26.5 | 33.2 | 0.298
aPneumothorax or pneumopericardium
bStudy discontinued when Treatment IND initiated
cNo cause of death in the SURVANTA group was significantly increased; the higher number of deaths in this group was due to the sum of all causes.

Rescue Studies

Infants of 600-1750 g birth weight with RDS requiring mechanical ventilation and an FiO2 ≥ 0.40 were enrolled in two multiple-dose rescue studies. The initial dose of SURVANTA was given after RDS developed and before 8 hours of age. Infants could receive up to three additional doses in the first 48 hours, as often as every 6 hours, if they required mechanical ventilation and an FiO2 ≥ 0.30. Results of the studies at 28 days of age are shown in Table 2.

Table 2.
Study 3 a
 | SURVANTA | Control | P-Value
Number infants studied | 198 | 193
Death due to RDS (%) | 11.6 | 18.1 | 0.071
Death or BPD due to RDS (%) | 59.1 | 66.8 | 0.102
Death due to any cause (%) | 21.7 | 26.4 | 0.285
Air Leaksb (%) | 11.8 | 29.5 | <0.001
Pulmonary interstitial emphysema (%) | 16.3 | 34.0 | <0.001

Study 4
 | SURVANTA | Control | P-Value
Number infants studied | 204 | 203
Death due to RDS (%) | 6.4 | 22.3 | < 0.001
Death or BPD due to RDS (%) | 43.6 | 63.4 | < 0.001
Death due to any cause (%) | 15.2 | 28.2 | 0.001
Air Leaksb (%) | 11.2 | 22.2 | 0.005
Pulmonary interstitial emphysema (%) | 20.8 | 44.4 | < 0.001
aStudy discontinued when Treatment IND initiated
bPneumothorax or pneumopericardium

Acute Clinical Effects

Marked improvements in oxygenation may occur within minutes of administration of SURVANTA.

All controlled clinical studies with SURVANTA provided information regarding the acute effects of SURVANTA on the arterial-alveolar oxygen ratio (a/APO2), FiO2, and mean airway pressure (MAP) during the first 48 to 72 hours of life. Significant improvements in these variables were sustained for 48-72 hours in SURVANTA-treated infants in four single-dose and two multiple-dose rescue studies and in two multiple-dose prevention studies. In the single-dose prevention studies, the FiO2 improved significantly.

INDICATIONS AND USAGE

SURVANTA is indicated for prevention and treatment (“rescue”) of Respiratory Distress Syndrome (RDS) (hyaline membrane disease) in premature infants.

CONTRAINDICATIONS

None

WARNINGS

SURVANTA can rapidly affect oxygenation and lung compliance within minutes of administration of SURVANTA. Therefore, its use should be restricted to a highly supervised clinical setting with immediate availability of clinicians experienced with intubation, ventilator management, and general care of premature infants. Infants receiving SURVANTA should be frequently monitored with arterial or transcutaneous measurement of systemic oxygen and carbon dioxide.

During the dosing procedure, transient episodes of bradycardia and decreased oxygen saturation have been reported. If these occur, stop the dosing procedure and initiate appropriate measures to alleviate the condition. After stabilization, resume the dosing procedure.

PRECAUTIONS

General

Rales and moist breath sounds can occur transiently after administration. Endotracheal suctioning or other remedial action is not necessary unless clear-cut signs of airway obstruction are present.

Increased probability of post-treatment nosocomial sepsis in SURVANTA-treated infants was observed in the controlled clinical trials (Table 3). The increased risk for sepsis among SURVANTA-treated infants was not associated with increased mortality among these infants. The causative organisms were similar in treated and control infants. There was no significant difference between groups in the rate of post-treatment infections other than sepsis.

Use of SURVANTA in infants less than 600 g birth weight or greater than 1750 g birth weight has not been evaluated in controlled trials. There is no controlled experience with use of SURVANTA in conjunction with experimental therapies for RDS (eg, high-frequency ventilation or extracorporeal membrane oxygenation).

No information is available on the effects of doses other than 100 mg phospholipids/kg, more than four doses, dosing more frequently than every 6 hours, or administration after 48 hours of age.

Carcinogenesis, Mutagenesis, Impairment of Fertility

Carcinogenicity studies have not been performed with SURVANTA. SURVANTA was negative when tested in the Ames test for mutagenicity. Using the maximum feasible dose volume, SURVANTA up to 500 mg phospholipids/kg/day (approximately one-third the premature infant dose based on mg/m^2/day) was administered subcutaneously to newborn rats for 5 days. The rats reproduced normally and there were no observable adverse effects in their offspring.

ADVERSE REACTIONS

The most commonly reported adverse experiences were associated with the dosing procedure. In the multiple-dose controlled clinical trials, each dose of SURVANTA was divided into four quarter-doses which were instilled through a catheter inserted into the endotracheal tube by briefly disconnecting the endotracheal tube from the ventilator. Transient bradycardia occurred with 11.9% of doses. Oxygen desaturation occurred with 9.8% of doses.

Other reactions during the dosing procedure occurred with fewer than 1% of doses and included endotracheal tube reflux, pallor, vasoconstriction, hypotension, endotracheal tube blockage, hypertension, hypocarbia, hypercarbia, and apnea. No deaths occurred during the dosing procedure, and all reactions resolved with symptomatic treatment.

The occurrence of concurrent illnesses common in premature infants was evaluated in the controlled trials. The rates in all controlled studies are in Table 3.

Table 3.
All Controlled Studies
Concurrent Event | SURVANTA (%) | Control (%) | P-Valuea
Patent ductus arteriosus | 46.9 | 47.1 | 0.814
Intracranial hemorrhage | 48.1 | 45.2 | 0.241
Severe intracranial hemorrhage | 24.1 | 23.3 | 0.693
Pulmonary air leaks | 10.9 | 24.7 | < 0.001
Pulmonary interstitial emphysema | 20.2 | 38.4 | < 0.001
Necrotizing enterocolitis | 6.1 | 5.3 | 0.427
Apnea | 65.4 | 59.6 | 0.283
Severe apnea | 46.1 | 42.5 | 0.114
Post-treatment sepsis | 20.7 | 16.1 | 0.019
Post-treatment infection | 10.2 | 9.1 | 0.345
Pulmonary hemorrhage | 7.2 | 5.3 | 0.166
a P-value comparing groups in controlled studies

When all controlled studies were pooled, there was no difference in intracranial hemorrhage. However, in one of the single-dose rescue studies and one of the multiple-dose prevention studies, the rate of intracranial hemorrhage was significantly higher in SURVANTA patients than control patients (63.3% v 30.8%, P = 0.001; and 48.8% v 34.2%, P = 0.047, respectively). The rate in a Treatment IND involving approximately 8100 infants was lower than in the controlled trials.

In the controlled clinical trials, there was no effect of SURVANTA on results of common laboratory tests: white blood cell count and serum sodium, potassium, bilirubin, and creatinine.

More than 4300 pretreatment and post-treatment serum samples from approximately 1500 patients were tested by Western Blot Immunoassay for antibodies to surfactant-associated proteins SP-B and SP-C. No IgG or IgM antibodies were detected.

Several other complications are known to occur in premature infants. The following conditions were reported in the controlled clinical studies. The rates of the complications were not different in treated and control infants, and none of the complications were attributed to SURVANTA.

Respiratory

lung consolidation, blood from the endotracheal tube, deterioration after weaning, respiratory decompensation, subglottic stenosis, paralyzed diaphragm, respiratory failure.

Cardiovascular

hypotension, hypertension, tachycardia, ventricular tachycardia, aortic thrombosis, cardiac failure, cardio-respiratory arrest, increased apical pulse, persistent fetal circulation, air embolism, total anomalous pulmonary venous return.

Gastrointestinal

abdominal distention, hemorrhage, intestinal perforations, volvulus, bowel infarct, feeding intolerance, hepatic failure, stress ulcer.

Renal

renal failure, hematuria.

Hematologic

coagulopathy, thrombocytopenia, disseminated intravascular coagulation.

Central Nervous System

seizures

Endocrine/Metabolic

adrenal hemorrhage, inappropriate ADH secretion, hyperphosphatemia.

Musculoskeletal

inguinal hernia.

Systemic

fever, deterioration.

Follow-Up Evaluations

To date, no long-term complications or sequelae of SURVANTA therapy have been found.

Single-Dose Studies

Six-month adjusted-age follow-up evaluations of 232 infants (115 treated) demonstrated no clinically important differences between treatment groups in pulmonary and neurologic sequelae, incidence or severity of retinopathy of prematurity, rehospitalizations, growth, or allergic manifestations.

Multiple-Dose Studies

Six-month adjusted age follow-up evaluations have been completed in 631 (345 treated) of 916 surviving infants. There were significantly less cerebral palsy and need for supplemental oxygen in SURVANTA infants than controls. Wheezing at the time of examination was significantly more frequent among SURVANTA infants, although there was no difference in bronchodilator therapy.

Final twelve-month follow-up data from the multiple-dose studies are available from 521 (272 treated) of 909 surviving infants. There was significantly less wheezing in SURVANTA infants than controls, in contrast to the six-month results. There was no difference in the incidence of cerebral palsy at twelve months.

Twenty-four month adjusted age evaluations were completed in 429 (226 treated) of 906 surviving infants. There were significantly fewer SURVANTA infants with rhonchi, wheezing, and tachypnea at the time of examination. No other differences were found.

OVERDOSAGE

Overdosage with SURVANTA has not been reported. Based on animal data, overdosage might result in acute airway obstruction. Treatment should be symptomatic and supportive.

Rales and moist breath sounds can transiently occur after SURVANTA is given, and do not indicate overdosage. Endotracheal suctioning or other remedial action is not required unless clear-cut signs of airway obstruction are present.

DOSAGE AND ADMINISTRATION

Important Administration Instructions

For intratracheal administration only.

SURVANTA should be administered by or under the supervision of clinicians experienced in intubation, ventilator management, and general care of premature infants. The administration of SURVANTA is facilitated if one person administers the dose while another person positions and monitors the infant.

Before administering SURVANTA, assure proper placement and patency of the endotracheal tube. At the discretion of the clinician, the endotracheal tube may be suctioned before administering SURVANTA. The infant should be allowed to stabilize before proceeding with dosing.

Administer SURVANTA intratracheally by instillation through a 5 French end-hole catheter.

Recommended Dosage

Each dose of SURVANTA is 100 mg of phospholipids/kg birth weight (4 mL/kg).

In the prevention strategy, in premature infants with evidence of surfactant deficiency, give the first dose of SURVANTA as soon as possible, preferably within 15 minutes of birth.

To treat infants with RDS confirmed by radiographic and clinical findings, give the first dose of SURVANTA as soon as possible, preferably by 8 hours of age.

Four doses of SURVANTA can be administered in the first 48 hours of life. Doses should be given no more frequently than every 6 hours.

The need for additional doses of SURVANTA is determined by evidence of continuing respiratory distress. Radiographic confirmation of RDS should be obtained before administering additional doses to those who received a prevention dose.

Preparation of the SURVANTA Suspension

SURVANTA should be inspected visually for discoloration prior to administration. The color of SURVANTA is off-white to light brown. If settling occurs during storage, swirl the vial gently (DO NOT SHAKE) to redisperse. Do not filter SURVANTA. Some foaming at the surface may occur during handling and is inherent in the nature of the product.

SURVANTA is stored refrigerated (36°F to 46°F [2°C to 8°C]). Date and time need to be recorded in the box on front of the carton or vial, whenever SURVANTA is removed from the refrigerator. Before administration, SURVANTA should be warmed by standing at room temperature for at least 20 minutes or warmed in the hand for at least 8 minutes. Artificial warming methods should not be used. If a prevention dose is to be given, preparation of SURVANTA should begin before the infant’s birth.

Unopened, unused vials of SURVANTA that have been warmed to room temperature may be returned to the refrigerator within 24 hours of warming, and stored for future use. SURVANTA SHOULD NOT BE REMOVED FROM THE REFRIGERATOR FOR MORE THAN 24 HOURS. SURVANTA SHOULD NOT BE WARMED AND RETURNED TO THE REFRIGERATOR MORE THAN ONCE. Each single-dose vial of SURVANTA should be entered only once. Used vials with residual drug should be discarded.

SURVANTA does not require reconstitution or sonication before use.

Administration

For endotracheal administration using a 5 French end-hole catheter:

1. Slowly withdraw the entire contents of the vial into a plastic syringe through a large-gauge needle (e.g., at least 20 gauge).

2. Attach the premeasured 5 French end-hole catheter to the syringe. Fill the catheter with SURVANTA. Discard excess SURVANTA through the catheter so that only the total dose to be given remains in the syringe.

3. When administering SURVANTA using a 5 French end-hole catheter, administer in four quarter-dose aliquots. Each quarter-dose is administered with the infant in a different position:

- Head and body inclined 5-10° down, head turned to the right
- Head and body inclined 5-10° down, head turned to the left
- Head and body inclined 5-10° up, head turned to the right
- Head and body inclined 5-10° up, head turned to the left

4. First quarter-dose aliquot of SURVANTA suspension:

a. Position the infant appropriately in one of the four recommended positions.

b. Insert the 5-French end-hole catheter into the endotracheal tube. The tip of the catheter should protrude just beyond the end of the endotracheal tube above the infant’s carina. SURVANTA should not be instilled into a mainstem bronchus.

c. Gently inject the first quarter-dose aliquot through the catheter over 2-3 seconds.

d. After the first aliquot is instilled, remove the catheter from the endotracheal tube and manually ventilate the infant for at least 30 seconds or until clinically stable. Ventilate with sufficient oxygen to prevent cyanosis and sufficient positive pressure to provide adequate air exchange and chest wall excursion.

5. When the infant is stable, reposition the infant for instillation of the next quarter-dose.

6. Instill each remaining quarter-dose using the same procedures.

7. After instillation of the final quarter-dose, remove the catheter without flushing it. Do not suction the infant for 1 hour after dosing unless signs of significant airway obstruction occur.

HOW SUPPLIED

SURVANTA (beractant) intratracheal suspension is supplied in 100 mg/4 mL single-dose glass vials (NDC 0074-1040-04) or 200 mg/8 mL single-dose glass vials (NDC 0074-1040-08). Each mL contains 25 mg of phospholipids suspended in 0.9% sodium chloride solution. The color is off-white to light brown.

Store unopened vials refrigerated at 36°F to 46°F (2°C to 8°C). Do not shake. Protect from light. Store vials in carton until ready for use. Vials are for one-time use and for only one patient. Upon opening, discard unused drug.

LITHO IN USA

AbbVie Inc.

North Chicago, IL 60064, U.S.A.

US License Number 1889

20065798 October, 2020

Principal Display Panel

NDC 0074-1040-08
8 mL One Single-Dose Vial
beractant
SURVANTA®
intratracheal suspension
200 mg/8 mL (25 mg/mL)

For Intratracheal
Administration Only

Sterile Suspension

Store refrigerated between
36 º F to 46 º F (2 º C to 8 º C).

DO NOT SHAKE.
PROTECT FROM LIGHT.

Rx only

abbvie

Principal Display Panel

NDC 0074-1040-04
4 mL One Single-Dose Vial
beractant
SURVANTA®
intratracheal suspension
100 mg/4 mL (25 mg/mL)

For Intratracheal
Administration Only

Sterile Suspension

Store refrigerated between
36 º F to 46 º F (2 º C to 8 º C).

DO NOT SHAKE.
PROTECT FROM LIGHT.

Rx only

abbvie